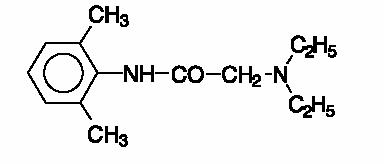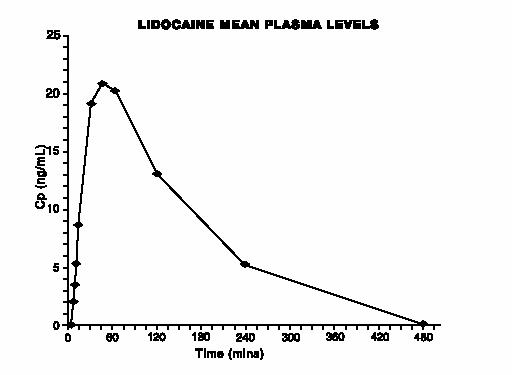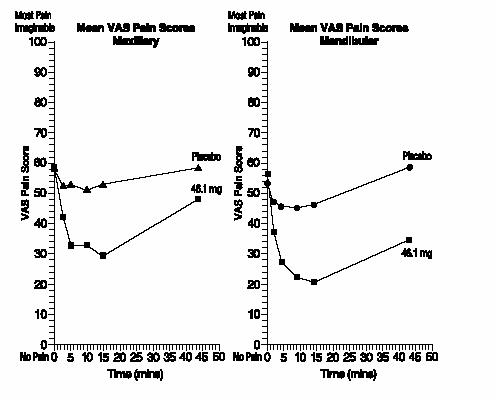 DRUG LABEL: Unknown
Manufacturer: Noven Parmaceuticals, Inc.
Category: prescription | Type: Human Prescription Drug Label
Date: 20060724

DentiPatch
(Lidocaine Transoral Delivery System)

DESCRIPTION

The DentiPatch® system contains a local anesthetic agent to be applied topically to the oral cavity. See INDICATIONS for specific uses.

Lidocaine is chemically designated as acetamide, 2-(diethylamino)-N-(2,6-dimethylphenyl)-, and has the following structural formula:

The molecular formula of lidocaine is C14H22N2O. The molecular weight is 234.34.

Each 2 cm^2 patch contains lidocaine base as the active ingredient in the amount of 46.1 mg. Non-active ingredients include: karaya gum, glycerin, dipropylene glycol, lecithin, propylene glycol, aspartame, spearmint flavor, polyester film laminate and polyester-rayon fabric.

Each unit is sealed in a paper polyethylene-foil pouch.

CLINICAL PHARMACOLOGY

Mechanism of action:

The DentiPatch® system is applied to the buccal mucosa to provide topical anesthesia by releasing lidocaine. Lidocaine stabilizes the neuronal membrane by inhibiting the ionic fluxes required for the initiation and conduction of impulses, thereby effecting local anesthetic action.

Onset and duration of action:

The DentiPatch® system acts on intact mucous membranes to produce local anesthesia.

DentiPatch® (Lidocaine Transoral Delivery System)

Anesthesia occurs usually within 2.5 minutes of application, is present for the duration of a 15 minute application period, and persists for approximately 30 minutes following removal.

Hemodynamics:

Excessive blood levels may cause changes in cardiac output, total peripheral resistance, and mean arterial pressure. These changes may be attributable to a direct depressant effect of the local anesthetic agent on various components of the cardiovascular system.

Pharmacokinetics and Metabolism:

Absorption

While systemic availability is not an objective when lidocaine is administered for topical anesthesia, limited absorption occurs following application of the patches to the buccal mucosa. The rate of absorption and percentage of dose absorbed depends upon several variables, including the concentration and total dose administered, the duration of exposure and the vascularity of the tissues at the site of application.

Although the total content of lidocaine base contained in each 2 cm^2 system is 46.1 mg, the total amount of drug absorbed during 15 minutes of application is limited as drug delivery is confined to a fixed surface area. Corresponding blood levels of lidocaine following application are less than 0.1 μg/ml. Assuming the toxic range of lidocaine is approximately 5 μg/ml, the maximum plasma concentration achieved from this patch is, therefore, approximately 1/100th of this value.

The figure shows the mean lidocaine plasma concentration following application of the 46.1 mg patch for 15 minutes to a group of normal male volunteers.

In this study, blood levels of lidocaine were compared following application of the patch and 5% Xylocaine® ointment. The maximum plasma concentration following the 46.1 mg patch was approximately 1/7 of those achieved by the ointment.

Another study compared the lidocaine plasma levels following applications of the patch, a 50 mg film of 5% topical ointment and an intravenous control in a cross-over design. The maximum plasma concentration following the 46.1 mg patch was approximately 1/5 of that achieved from the intravenous dose. The relevant mean pharmacokinetic parameters from this study are summarized in the table below. In addition, the table also indicates the range of AUC's obtained in two independent studies.

MEAN (±SD) PHARMACOKINETIC PARAMETERS OBTAINED FOLLOWING APPLICATION OF THE DENTIPATCH® SYSTEM FOR 15 MINUTES
PHARMACOKINETIC PARAMETERS
Lidocaine content (mg) | Cmax (ng/mL) | Tmax (min) | Apparent Dose (mg) | t1/2 min | AUC0-α (ng•min/mL) Study 3005 Study 3006
46.1 | 16.5 (±7.9) | 28.6 (±12.9) | 1.55 (±0.77) | 102 (±25) | 2110 (±930) | 3679 (±1432)
Cmax = Maximum observed plasma concentration.
Tmax = Time to maximum plasma concentration.
Apparent dose = Calculated dose (estimated from the AUC0-α values and the known IV dose).
t1/2=Apparent terminal elimination half-life.

The apparent dose of lidocaine averaged 1.55 (± 0.77) mg from the 46.1 mg dosage. This compares to an apparent dose of 3.77 (±2.71) mg from the 5% topical ointment and 4.79 (±0.79) mg from the intravenous drug. In this study, the half-life of elimination of lidocaine following the patch was approximately 2 hours compared to a mean half-life of 112 (±20) minutes following the IV drug.

Metabolism and Excretion

Lidocaine is metabolized rapidly by the liver and metabolites and unchanged drug are excreted by the kidney.

Biotransformation includes oxidative N-dealkylation, ring hydroxylation, cleavage of the amide linkage, and conjugation (the hepatic ratio for lidocaine has been reported between 62% and 81% in man). Sequential oxidative N-dealkylation of lidocaine by the cytochrome P-450 system in hepatic microsomes produce two major metabolites, mono-ethylglyciniexylidide (MEGX) and glycine xylidide (GX), both of which have pharma-cologic activity.

Greater than 98% of an administered lidocaine dose can be recovered in the urine as metabolites and parent compound. Approximately 2% of an administered dose is excreted as intact drug in the urine over 24 hours. The primary metabolite found in the urine was 4-hydroxy 2, 6-xylidine, which comprised 73% of the dose in man following an oral dose of 3.0 mg/kg, MEGX and GX are found in small quantities: 4.0% and 2.5%, respectively. Other metabolic products recovered in the urine in amounts of less than 1.0% of an administered dose include 3-hydroxylidocaine, 3-hydroxyMEGX, and 2.6-xylidine. The metabolite 2,6-xylidine has unknown pharmacologic activity but has been demonstrated to be carcinogenic in rats. (See Carcinogenesis subsection of PRECAUTIONS).

Lidocaine crosses the blood-brain and placental barriers, presumably by passive diffusion. Factors such as acidosis and the use of CNS stimulants and depressants affect the CNS levels of lidocaine required to produce overt systemic effects. Objective adverse manifestations become increasingly apparent with increasing venous plasma levels above 6.0 μg free base per mL.

The extent of lidocaine protein binding is variable and is dependent upon the method of sample collection, lidocaine concentration, pH of sample and binding technique utilized. Under controlled conditions and using equilibrium dialysis techniques, the percentage of unbound lidocaine in serum and plasma has been reported to range from 21% to 39% (mean 28-30%). The major binding site of lidocaine in plasma is alpha,-1 acid glycoprotein.

Special Populations

Geriatric

No special studies have been conducted in this age group.

Pediatric

No special studies have been conducted in the pediatric age group.

Gender

No significant differences in absorption, etc. have been found in males and females. In a group of 30 volunteers (16 female, 14 male) receiving the 46.1 mg patch, the observed maximum plasma concentrations were 27.2 (±15.2) ng/mL at 45 (±12.5) minutes following application. Mean maximum concentrations were 31.5 (±17.4) ng/mL in females and 22.2 (±10.6) ng/mL in males.

Race

No specific studies were conducted comparing the pharmacokinetics in different races.

Renal Insufficiency

Renal dysfunction does not affect lidocaine kinetics but may increase the accumulation of metabolites.

Hepatic Insufficiency

Because of the rapid rate at which lidocaine is metabolized, any condition that affects liver function may alter lidocaine kinetics. The half-life may be prolonged two-fold or more in patients with liver dysfunction.

Drug-Drug Interactions

Lidocaine is metabolized by cytochrome P450 3A4-7 and 2D6. Inhibitors of these enzymes by H2 antagonists, antibiotics or some antiepileptics may elevate systemic lidocaine levels resulting in a prolonged effect.

CLINICAL STUDIES

The DentiPatch® system was studied in 275 volunteers who underwent needle insertion during four clinical studies. Application of the 46.1 mg patch for 15 minutes to the maxillary mucosae provided significantly more buccal anesthesia than a corresponding placebo at 5, 10, and 15 minutes.

Similar findings were also observed following application of the patch to placement sites on both the maxillary and mandibular buccal mucosae. In one large, multi-center trial consisting of 100 subjects, differences in responsiveness to the 46.1 mg patch compared to placebo were assessed following application of the patches for 15-minute periods to each of these placement sites. Assessments were made at 2.5, 5, 10, and 15 minutes during application and again at 45 minutes.

For the mandibular placement sites, statistically significant decreases in pain scores from baseline were observed at 2.5, 5, 10, 15, and 45 minutes post-application. For each time point, the decrease in pain score for the 46.1 mg lidocaine group was statistically significantly greater than placebo. For the maxillary placement sites, statistically significant decreases in the pain scores were observed at 5, 10, 15, and 45 minutes for the 46.1 mg group, but was not statistically significantly different from placebo at 2.5 minutes.

The mean change in visual analog scores (VAS) from baseline at these two sites for the 46.1 mg group and placebo are shown for each time point in the figures below.

Mean Change In VAS Scores

The mean plasma concentrations of lidocaine which were observed following application of the active dosage at these time points showed little difference between mandibular and maxillary placement sites.

INDICATIONS AND USAGE

The DentiPatch® system is indicated for the production of mild topical anesthesia of the accessible mucous membranes of the mouth prior to superficial dental procedures. It may also reduce the pain associated with injections of local anesthetic into the gingiva.

CONTRAINDICATIONS

Lidocaine is contraindicated in patients with a known history of hypersensitivity to local anesthetics of the amide type or to other components of the DentiPatch® system.

WARNINGS

IN ORDER TO MANAGE POSSIBLE ADVERSE REACTIONS, RESUSCITATIVE EQUIPMENT, OXYGEN AND OTHER RESUSCITATIVE DRUGS MUST BE IMMEDIATELY AVAILABLE WHEN LOCAL ANESTHETIC AGENTS, SUCH AS LIDOCAINE, ARE ADMINISTERED TO MUCOUS MEMBRANES.

The DentiPatch® system should be used with extreme caution if there is sepsis or extremely traumatized mucosa in the area of application, since under such conditions there is the potential for rapid systemic absorption.

PRECAUTIONS

General

The safety and effectiveness of lidocaine depend on proper dosage, correct technique, adequate precautions, and readiness for emergencies. Resuscitative equipment, oxygen, and other resuscitative drugs should be available for immediate use. (See WARNINGS and ADVERSE REACTIONS.) The lowest dosage that results in effective anesthesia should be used to avoid high plasma levels and serious adverse effects. Repeated doses of lidocaine may cause significant increases in blood levels with each repeated dose because of slow accumulation of the drug or its metabolites. Tolerance varies with the status of the patient. Debilitated, elderly patients, acutely ill patients, and children should be given reduced doses commensurate with their age and physical status. Lidocaine should also be used with caution in patients with severe shock or heart block.

The DentiPatch® system should be used with caution in patients with known drug sensitivities. Patients allergic to para-aminobenzoic acid derivatives (procaine, tetracaine, benzocaine, etc.) have not shown cross sensitivity to lidocaine.

Many drugs used during the conduct of anesthesia are considered potential triggering agents for familial malignant hyperthermia. Since it is not known whether amide-type local anesthetics may trigger this reaction and since the need for supplemental general anesthesia cannot be predicted in advance, it is suggested that a standard protocol for management should be available. Early unexplained signs of tachycardia, tachypnea, labile blood pressure and metabolic acidosis may precede temperature elevation. Successful outcome is dependent on early diagnosis, prompt discontinuance of the suspect triggering agent(s) and institution of treatment, including oxygen therapy, indicated supportive measures and dantrolene (consult dantrolene sodium intravenous package insert before using).

Information for patients

Use of the DentiPatch® system is frequently associated with mild local redness and infrequently with the development over a day or so of more severe local reactions. While these reactions are expected to resolve spontaneously, the concerned patient should be encouraged to report them to the practitioner.

Carcinogenesis, mutagenesis, impairment of fertility

Carcinogenesis: Long term study in animals to evaluate the carcinogenic potential of lidocaine has not been conducted.

A two-year oral toxicity study of 2,6-xylidine, a metabolite of lidocaine, conducted in both male and female rats, has shown that daily doses of 900 mg/m^2 (150 mg/kg) resulted in carcinomas and adenomas of the nasal cavity. With daily doses of 300 mg/m^2 (50 mg/kg), the increase in incidence of nasal carcinomas and/or adenomas in each sex of the rat were not statistically greater than the control group. In the low dose group of 90 mg/m^2 (15 mg/kg) and control, no nasal tumors were observed. A rhabdomyosarcoma, a rare tumor, was observed in the nasal cavity of both male and female rats at the high dose of 900 mg/m^2 (150 mg/kg). In addition, the compound caused subcutaneous fibromas and/or fibrosarcomas in both male and female rats and neoplastic nodules of the liver in the female rats with a significantly positive trend test; pairwise comparisons using Fisher's Exact Test showed significance only at the high dose of 900 mg/m^2 (150 mg/kg).

Mutagenesis: The mutagenic potential of lidocaine HCI has been tested in the Ames Salmonella/mammalian microsome test and by analysis of structural chromosome aberrations in human lymphocytes in vitro, and by the mouse micronucleus test in vivo. There was no indication in these three tests of any mutagenic effects.

The mutagenicity of 2,6-xylidine, a metabolite of lidocaine, has been studied in different tests with mixed results. The compound was found to be weakly mutagenic in the Ames test only under metabolic activation conditions. In addition, 2,6-xylidine was observed to be mutagenic at the thymidine kinase locus, with or without activation, and induced chromosome aberrations and sister chromatid exchanges at concentrations at which the drug precipitated out of the solution (1.2 mg/mL). No evidence of genotoxicity was found in the in vivo assays measuring unscheduled DNA synthesis in rat hepatocytes, chromosome damage in polychromatic erythrocytes or preferential killing of DNA repair-deficient bacteria in liver, lung, kidney, testes and blood extracts from mice. However, covalent binding studies of DNA from liver and ethmoid turbinates in rats indicate that 2,6-xylidine may be genotoxic under certain conditions in vivo.

Use in Pregnancy

Teratogenic Effects. Pregnancy Category B. Reproduction studies have been performed in rats at doses up to 6.6 times the human dose and have revealed no evidence of harm to the fetus caused by lidocaine. There are, however, no adequate and well-controlled studies in pregnant women. Animal reproduction studies are not always predictive of human response. General consideration should be given to this fact before administering lidocaine to women of childbearing potential, especially during early pregnancy when maximum organogenesis takes place.

Nursing mothers

It is not known whether this drug is excreted in human milk. Because many drugs are excreted in human milk, caution should be exercised when lidocaine is administered to a nursing woman.

Pediatric use

Safety and effectiveness in children below the age of 12 years have not been established.

Phenylketonurics

Contains phenylalanine 0.62 mg per system.

ADVERSE REACTIONS

Localized Reactions: During controlled clinical trials with this dosage form, the area of patch application was evaluated for oral irritation following removal. In the majority of instances, no irritation was observed. Minimal to moderate redness was reported, however, in fewer than 15% of the applications of the patch and placebo.

General Adverse Events: In controlled clinical trials, the percentage of subjects reporting adverse events was similar in the two treatment groups consisting of the 46.1 mg and placebo patches. Overall, the most frequently occurring adverse experiences irrespective of causality were taste perversion, stomatitis (including erythema and other types of mucosal reactions), headache and gingivitis.

The incidence of drug-related (definite, probably/highly probably) events was low in both treatment groups, however.

Other adverse experiences reported following the administration of lidocaine are similar in nature to those observed with other amide local anesthetic agents. These adverse experiences are, in general, dose-related and may result from high plasma levels caused by excessive dosage or rapid absorption, or may result from a hypersensitivity, idiosyncrasy or diminished tolerance on the part of the patient. Serious adverse experiences are generally systemic in nature. The following types are the most common reported.

Central nervous system: CNS manifestations are excitatory and/or depressant and may be characterized by lightheaded-ness, nervousness, apprehension, euphoria, confusion, dizziness, drowsiness, tinnitus, blurred or double vision, vomiting, sensations of heat, cold or numbness, twitching, tremors, convulsions, unconsciousness, respiratory depression and arrest. The excitatory manifestations may be very brief or may not occur at all, in which case the first manifestation of toxicity may be drowsiness merging into unconsciousness and respiratory arrest.

Drowsiness following the administration of lidocaine is usually an early sign of a high blood level of the drug and may occur as a consequence of rapid absorption:

Cardiovascular system:Cardiovascular manifestations are usually depressant and are characterized by bradycardia, hypotension, and cardiovascular collapse, which may lead to cardiac arrest.

Allergic: Allergic reactions are characterized by cutaneous lesions, urticaria, edema or anaphylactoid reactions. Allergic reactions may occur as a result of sensitivity either to the local anesthetic agent or to other ingredients in the formulation. Allergic reactions as a result of sensitivity to lidocaine are extremely rare and, if they occur, should be managed by conventional means. The detection of sensitivity by skin testing is of doubtful value.

OVERDOSAGE

Acute emergencies from local anesthetics are generally related to high plasma levels encountered during therapeutic use of local anesthetics. (See ADVERSE REACTIONS, WARNINGS, and PRECAUTIONS.)

Management of local anesthetic emergencies: The first consideration is prevention, best accomplished by careful and constant monitoring of cardiovascular and respiratory vital signs and the patient's state of consciousness after each local anesthetic administration. At the first sign of change, oxygen should be administered.

The first step in the management of convulsions consists of immediate attention to the maintenance of a patent airway and assisted or controlled ventilation with oxygen and a delivery system capable of permitting immediate positive airway pressure by mask. Immediately after the institution of these ventilatory measures, the adequacy of the circulation should be evaluated, keeping in mind that drugs used to treat convulsions sometimes depress the circulation when administered intravenously. Should convulsions persist despite adequate respiratory support, and if the status of the circulation permits, small increments of an ultra-short acting barbiturate (such as thiopental or thiamylal) or a benzodiazepine (such as diazepam) may be administered intravenously. The clinician should be familiar, prior to use of local anesthetics, with these anticonvulsant drugs. Supportive treatment of circulatory depression may require administration of intravenous fluids and, when appropriate, a vasopressor as directed by the clinical situation (e.g., ephedrine).

If not treated immediately, both convulsions and cardiovascular depression can result in hypoxia, acidosis, bradycardia, arrhythmias and cardiac arrest. If cardiac arrest should occur, standard cardiopulmonary resuscitative measures should be instituted.

Dialysis is of negligible value in the treatment of acute overdosage with lidocaine.

DOSAGE AND ADMINISTRATION

When the DentiPatch® system is used concomitantly with other products containing lidocaine, the total dose contributed by all formulations must be kept in mind.

Isolate the procedure area with cotton rolls and use suction as appropriate. Dry the tissue with air or gauze. Remove the DentiPatch® system from its packaging and peel off the clear protective liner. Immediately apply the DentiPatch® system using firm pressure. Allow the patch to remain in place until the desired anesthetic effect is produced but not for longer than 15 minutes. Experience in children is inadequate to recommend a pediatric dose at this time.

HOW SUPPLIED

DentiPatch® system (46.1 mg/unit) - each 2.0 cm^2 system contains 46.1 mg of lidocaine USP.

Dispenser carton of 50 systems NDC 57616-041-12

Do not store above 25°C.
Keep out of the reach of children.

May 1999
Package Insert
Noven Parmaceuticals, Inc.
100956-1

Manufactured by:
Noven Pharmaceuticals, Inc.
Miami, Florida 33186